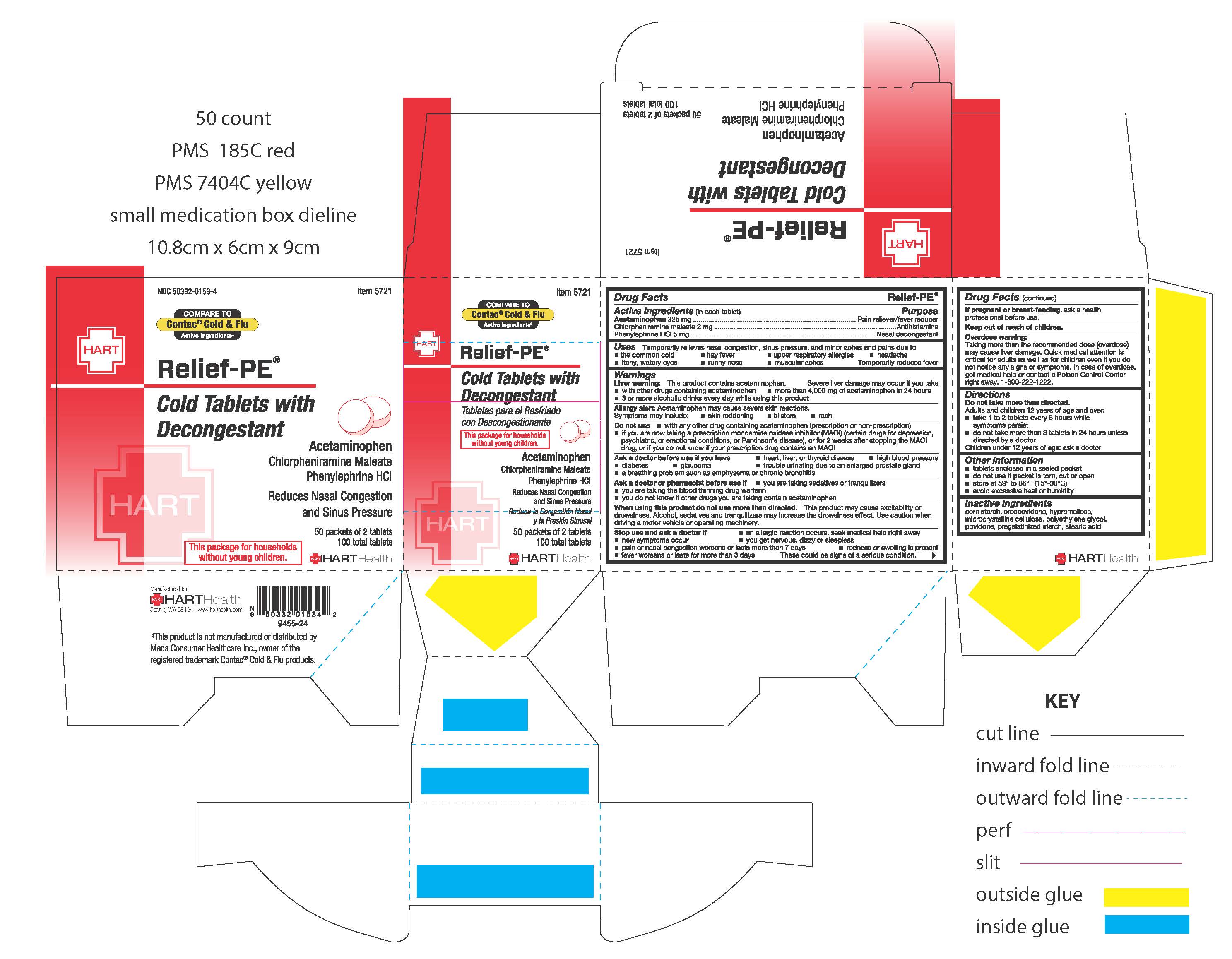 DRUG LABEL: Relief-PE
NDC: 50332-0153 | Form: TABLET, COATED
Manufacturer: HART Health
Category: otc | Type: HUMAN OTC DRUG LABEL
Date: 20260115

ACTIVE INGREDIENTS: ACETAMINOPHEN 325 mg/1 1; PHENYLEPHRINE HYDROCHLORIDE 5 mg/1 1; CHLORPHENIRAMINE MALEATE 2 mg/1 1
INACTIVE INGREDIENTS: STARCH, CORN; STEARIC ACID; CROSPOVIDONE; MICROCRYSTALLINE CELLULOSE; HYPROMELLOSES; POLYETHYLENE GLYCOL, UNSPECIFIED; POVIDONE

Relief-PE

Active Ingredients (in each tablet):

Acetaminophen 325mg

Phenylephrine HCl 5mg

Chlorpheniramine Maleate 2mg

Purpose:

Pain Reliever/Fever Reducer

Antihistamine

Nasal Decongestant

INDICATIONS AND USAGE

Temporarily relieves nasal congestion, sinus pressure, and minor aches and pains due to:

- the common cold
- hay fever
- upper respiratory allergies
- headache
- itchy/watery eyes
- runny nose
- muscular aches

Temporarily reduces fever

WARNINGS

Liver warning: this product contains acetaminophen. Severe liver damage may occur if you take:

- more than 4000mg of acetaminophen 24 hours
- with other drugs containing acetaminophen
- 3 or more alcohol drinks every day while using this product

Allergy alert: acetaminophen may cause severe skin reactions. Symptoms may include:

- skin reddening
- blisters
- rash

Do not use:

- with any other drug containing acetaminophen (prescription or non-prescription)
- if you are now taking a prescription monoamine oxidase inhibitor (MAOI) (certain drugs for depression, psychiatric, or emotional conditions, or Parkinson's disease), or for 2 weeks after stopping the MAOI drug, or if you do not know if your prescription drug contains an MAOI

Ask a doctor or pharmacist before use if

- you are taking sedatives or tranquilizers
- you are taking the blood thinning drug warfarin
- you do not know if other drugs you are taking contain acetaminophen

Ask a doctor before use if you have

- heart, liver, or thyroid disease
- high blood pressure
- diabetes
- glaucoma
- trouble urinating due to an enlarged prostate gland
- a breathing problem such as emphysema or chronic bronchitis

When using this product to not use more than directed. This product may cause excitability or drowsiness. Alcohol, sedatives and tranquilizers may increase the drowsiness effect. Use caution when driving a motor vehicle or operating machinery.

Stop use and ask a doctor if

- an allergic reaction occurs, seek medical help right away
- you get nervous, dizzy or sleepless
- new symptom occur
- fever worsens or lasts for more than 3 days
- pain or nasal congestion gets worse or lasts more than 7 days
- redness or swelling is present

These could be signs of serious condition

PREGNANCY OR BREAST FEEDING

If pregnant or breast-feeding, ask a health professional before use.

Keep out of reach of children.

OVERDOSAGE

Overdose warning:

Taking more than the recommended dose (overdose) may cause liver damage. Quick medical attention is critical for adults as well as for children even if you do not notice any signs or symptoms. In case of overdose, get medical help or contact a Poison Control Center right away. 1-800-222-1222.

DOSAGE AND ADMINISTRATION

Directions: Do not take more than directed. Adults and children 12 years of age an over:

- take 1 to 2 tablets every 6 hours while symptoms persist
- do not take more than 8 tablets in 24 hours unless directed by a doctor

Children under 12 years of age: ask a doctor

INACTIVE INGREDIENT

corn starch, crospovidone, hypromellose, microcrystalline cellulose, polyethylene glycol, povidone, pregelantined starch, stearic acid